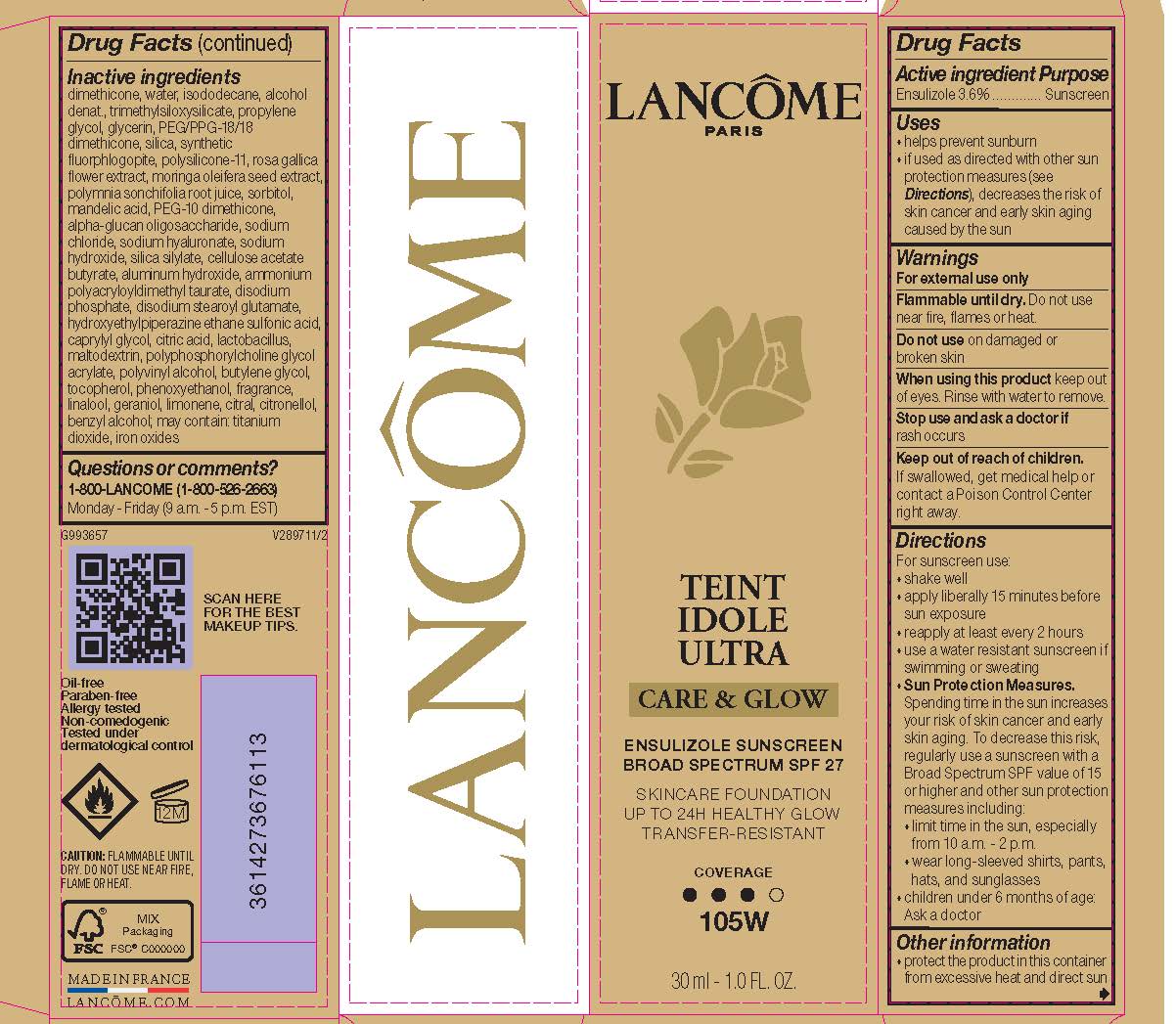 DRUG LABEL: Lancome Paris Teint Idole Ultra Care and Glow Skincare Foundation Broad Spectrum SPF 27 Sunscreen
NDC: 49967-676 | Form: LIQUID
Manufacturer: L'Oreal USA Products Inc
Category: otc | Type: HUMAN OTC DRUG LABEL
Date: 20240625

ACTIVE INGREDIENTS: ENSULIZOLE 36 mg/1 mL
INACTIVE INGREDIENTS: DIMETHICONE; WATER; ISODODECANE; ALCOHOL; TRIMETHYLSILOXYSILICATE (M/Q 0.6-0.8); PROPYLENE GLYCOL; GLYCERIN; PEG/PPG-18/18 DIMETHICONE; SILICON DIOXIDE; MAGNESIUM POTASSIUM ALUMINOSILICATE FLUORIDE; DIMETHICONE/VINYL DIMETHICONE CROSSPOLYMER (SOFT PARTICLE); ROSA GALLICA FLOWER; SORBITOL; MANDELIC ACID; PEG-10 DIMETHICONE (600 CST); .ALPHA.-GLUCAN OLIGOSACCHARIDE; SODIUM CHLORIDE; HYALURONATE SODIUM; SODIUM HYDROXIDE; ALUMINUM HYDROXIDE; AMMONIUM POLYACRYLOYLDIMETHYL TAURATE (55000 MPA.S); SODIUM PHOSPHATE, DIBASIC, ANHYDROUS; DISODIUM STEAROYL GLUTAMATE; HYDROXYETHYLPIPERAZINE ETHANE SULFONIC ACID; CAPRYLYL GLYCOL; CITRIC ACID MONOHYDRATE; MALTODEXTRIN; POLYVINYL ALCOHOL, UNSPECIFIED; BUTYLENE GLYCOL; TOCOPHEROL; PHENOXYETHANOL; LINALOOL, (+/-)-; GERANIOL; LIMONENE, (+)-; CITRAL; .BETA.-CITRONELLOL, (R)-; BENZYL ALCOHOL; TITANIUM DIOXIDE; FERRIC OXIDE RED

Drug Facts

Active ingredient

Ensulizole 3.6%

Purpose

Sunscreen

Uses

- helps prevent sunburn
- if used as directed with other sun protection measures (see Directions), decreases the risk of skin cancer and early skin aging caused by the sun

Warnings

For external use only

Flammable until dry.

Do not use near fire, flame, or heat.

Do not use

on damaged or broken skin

When using this product

keep out of eyes. Rinse with wate to remove.

Stop use and ask a doctor if

rash occurs

Keep out of reach of children.

If swallowed, get medical help or contact a Poison Control Center right away.

Directions

For sunscreen use:

● shake well

● apply liberally 15 minutes before sun exposure

● reapply at least every 2 hours

● use a water resistant sunscreen if swimming or sweating

● Sun Protection Measures. Spending time in the sun increases your risk of skin cancer and early skin aging. To decrease this risk, regularly use a sunscreen with a Broad Spectrum SPF value of 15 or higher and other sun protection measures including:

● limit time in the sun, especially from 10 a.m. – 2 p.m.

● wear long-sleeved shirts, pants, hats, and sunglasses

● children under 6 months of age: Ask a doctor

Other information

protect the product in this container from excessive heat and direct sun

Inactive ingredients

dimethicone, water, isododecane, alcohol denat., trimethylsiloxysilicate, propylene glycol, glycerin, PEG/PPG-18/18 dimethicone, silica, synthetic fluorphlogopite, polysilicone-11, rosa gallica flower extract, moringa oleifera seed extract, polymnia sonchifolia root juice, sorbitol, mandelic acid, PEG-10 dimethicone, alpha-glucan oligosaccharide. sodium chloride, sodium hyaluronate, sodium hydroxide, silica silylate, cellulose acetate butyrate, aluminum hydroxide, ammonium polyacryloyldimethyl taurate, disodium phosphate, disodium stearoyl glutamate, hydroxyethylpiperazine ethane sulfonic acid, caprylyl glycol, citric acid, lactobacillus, maltodextrin, polyphosphorylcholine glycol acrylate, polyvinyl alcohol, butylene glycol, tocopherol, phenoxyethanol, fragrance, linalool, geraniol, limonene, citral, citronellol, benzyl alcohol; may contain: titanium dioxide, iron oxides

Questions or comments?

1-800-LANCOME

(1-800-526-2663)

Monday - Friday

(9 a.m. - 5 p.m. EST)